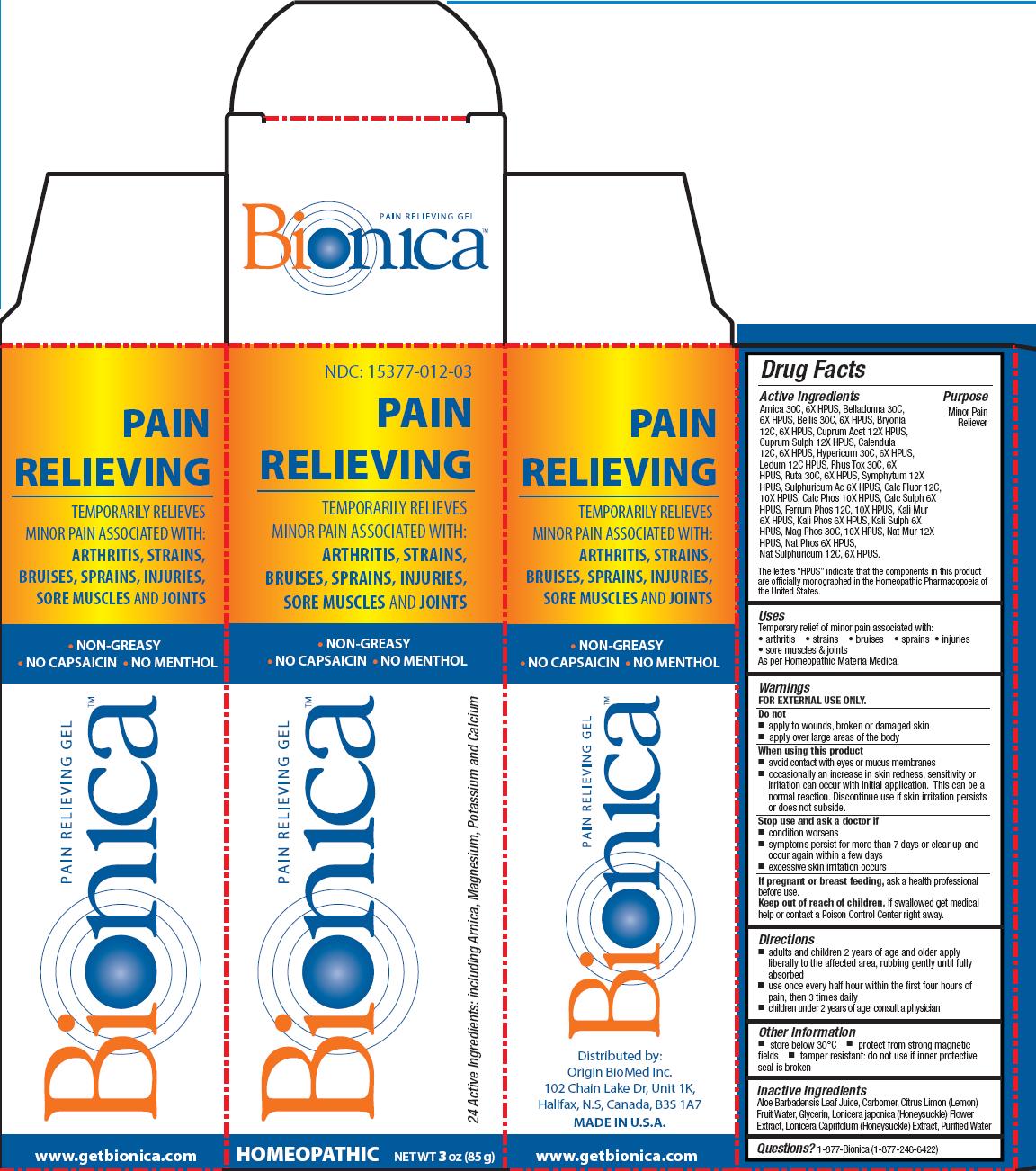 DRUG LABEL: Bionica Pain Relieving Gel
                
NDC: 15377-012 | Form: GEL
Manufacturer: Origin BioMed Inc.
Category: homeopathic | Type: HUMAN OTC DRUG LABEL
Date: 20140523

ACTIVE INGREDIENTS: ARNICA MONTANA FLOWER 30 [hp_C]/85 g; ATROPA BELLADONNA 30 [hp_C]/85 g; BELLIS PERENNIS 30 [hp_C]/85 g; BRYONIA ALBA ROOT 12 [hp_C]/85 g; CUPRIC ACETATE 12 [hp_X]/85 g; CUPRIC SULFATE 12 [hp_X]/85 g; CALENDULA OFFICINALIS FLOWERING TOP 12 [hp_C]/85 g; HYPERICUM PERFORATUM 30 [hp_C]/85 g; LEDUM PALUSTRE TWIG 12 [hp_C]/85 g; TOXICODENDRON PUBESCENS LEAF 30 [hp_C]/85 g; RUTA GRAVEOLENS FLOWERING TOP 30 [hp_C]/85 g; COMFREY ROOT 12 [hp_X]/85 g; SULFURIC ACID 6 [hp_X]/85 g; CALCIUM FLUORIDE 12 [hp_C]/85 g; TRIBASIC CALCIUM PHOSPHATE 10 [hp_X]/85 g; CALCIUM SULFATE ANHYDROUS 6 [hp_X]/85 g; FERROSOFERRIC PHOSPHATE 12 [hp_C]/85 g; POTASSIUM CHLORIDE 6 [hp_X]/85 g; POTASSIUM PHOSPHATE, DIBASIC 6 [hp_X]/85 g; POTASSIUM SULFATE 6 [hp_X]/85 g; MAGNESIUM PHOSPHATE, DIBASIC TRIHYDRATE 30 [hp_C]/85 g; SODIUM SULFATE 12 [hp_C]/85 g; SODIUM CHLORIDE 12 [hp_X]/85 g; SODIUM PHOSPHATE, DIBASIC, HEPTAHYDRATE 6 [hp_X]/85 g
INACTIVE INGREDIENTS: ALOE VERA LEAF; GLYCERIN; LONICERA JAPONICA FLOWER; LONICERA CAPRIFOLIUM FLOWER; WATER

Drug Facts

Active Ingredients

Arnica 30C, 6X HPUS, Belladonna 30C,6X HPUS, Bellis 30C, 6X HPUS, Bryonia 12C, 6X HPUS, Cuprum Acet 12X HPUS,Cuprum Sulph 12X HPUS, Calendula 12C, 6X HPUS, Hypericum 30C, 6X HPUS, Ledum 12C HPUS, Rhus Tox 30C, 6X HPUS, Ruta 30C, 6X HPUS, Symphytum 12X HPUS, Sulphuricum Ac 6X HPUS, Calc Fluor 12C,10X HPUS, Calc Phos 10X HPUS, Calc Sulph 6X HPUS, Ferrum Phos 12C, 10X HPUS, Kali Mur 6X HPUS, Kali Phos 6X HPUS, Kali Sulph 6X HPUS, Mag Phos 30C, 10X HPUS, Nat Mur 12X HPUS, Nat Phos 6X HPUS, Nat Sulphuricum 12C, 6X HPUS.

The letters “HPUS” indicate that the components in this product are officially monographed in the Homeopathic Pharmacopoeia of the United States

Purpose

Minor Pain Reliever

Uses

Temporary relief of minor pain associated with:
• arthritis • strains • bruises • sprains • injuries
• sore muscles and joints
As per Homeopathic Materia Medica.

Warnings

FOR EXTERNAL USE ONLY.

Do not

- apply to wounds, broken or damaged skin
- apply over large areas of the body

When using this product

- avoid contact with eyes or mucus membranes
- occasionally an increase in skin redness, sensitivity or irritation can occur with initial application. This can be a normal reaction. Discontinue use if skin irritation persists or does not subside.

Stop use and ask a doctor if

- condition worsens
- symptoms persist for more than 7 days or clear up and occur again within a few days
- excessive skin irritation occurs

PREGNANCY OR BREAST FEEDING

If pregnant or breast feeding,ask a health professional before use.

Keep out of reach of children. If swallowed get medical help or contact a Poison Control Center right away.

Directions

- adults and children 2 years of age and older apply liberally to the affected area, rubbing gently until fully absorbed
- use once every half hour within the first four hours of pain, then 3 times daily
- children under 2 years of age: consult a physician

Other Information

- store below 30°C
- protect from strong magnetic fields
- tamper resistant: do not use if inner protective seal is broken

Inactive Ingredients

Aloe Barbadensis Leaf Juice, Carbomer, Citrus Lemon (Lemon) Fruit Water, Glycerin, Lonicera japonica (Honeysuckle) Flower Extract, Lonifera Caprifolum (Honeysuckle) Extract, Purified Water

Questions?

1-877-Bionica (1-877-246-6422)

DESCRIPTION

Distributed by:
Origin BioMed Inc.
102 Chain Lake Dr, Unit 1K,
Halifax, N.S, Canada, B3S 1A7
MADE IN U.S.A.
www.getbionica.com

Principal Display Panel

NDC: 15377-012-03
PAIN RELIEVING

TEMPORARILY RELIEVES MINOR PAIN ASSOCIATED WITH:
ARTHRITIS, STRAINS, BRUISES, SPRAINS, INJURIES, SORE MUSCLES AND JOINTS
• NON-GREASY
• NO CAPSAICIN
• NO MENTHOL
24 Active Ingredients: including Arnica, Magnesium, Potassium and Calcium
HOMEOPATHIC

NET WT 3 oz (85 g)